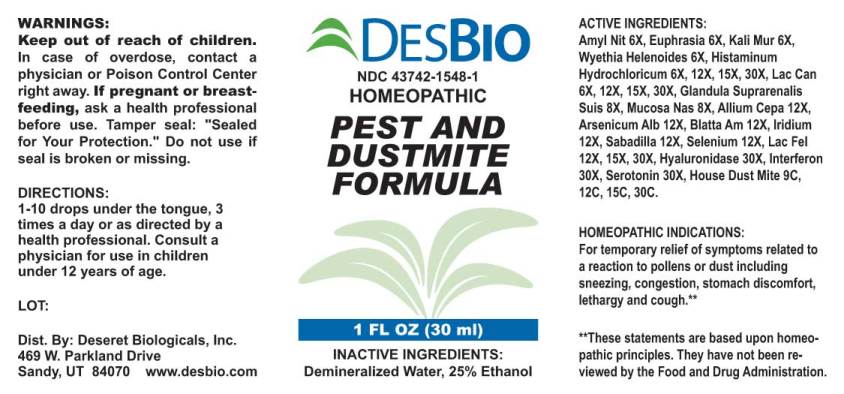 DRUG LABEL: Pest and Dustmite Formula
NDC: 43742-1548 | Form: LIQUID
Manufacturer: Deseret Biologicals, Inc.
Category: homeopathic | Type: HUMAN OTC DRUG LABEL
Date: 20240927

ACTIVE INGREDIENTS: AMYL NITRITE 6 [hp_X]/1 mL; EUPHRASIA STRICTA 6 [hp_X]/1 mL; POTASSIUM CHLORIDE 6 [hp_X]/1 mL; WYETHIA HELENIOIDES ROOT 6 [hp_X]/1 mL; HISTAMINE DIHYDROCHLORIDE 6 [hp_X]/1 mL; CANIS LUPUS FAMILIARIS MILK 6 [hp_X]/1 mL; SUS SCROFA ADRENAL GLAND 8 [hp_X]/1 mL; SUS SCROFA NASAL MUCOSA 8 [hp_X]/1 mL; ONION 12 [hp_X]/1 mL; ARSENIC TRIOXIDE 12 [hp_X]/1 mL; PERIPLANETA AMERICANA 12 [hp_X]/1 mL; IRIDIUM 12 [hp_X]/1 mL; SCHOENOCAULON OFFICINALE SEED 12 [hp_X]/1 mL; SELENIUM 12 [hp_X]/1 mL; FELIS CATUS MILK 12 [hp_X]/1 mL; HYALURONIDASE 30 [hp_X]/1 mL; INTERFERON .GAMMA. PORCINE RECOMBINANT 30 [hp_X]/1 mL; SEROTONIN HYDROCHLORIDE 30 [hp_X]/1 mL; DERMATOPHAGOIDES FARINAE 9 [hp_C]/1 mL
INACTIVE INGREDIENTS: WATER; ALCOHOL

Drug Facts:

ACTIVE INGREDIENTS:

Amyl Nitrosum 6X, Euphrasia Officinalis 6X, Kali Muriaticum 6X, Wyethia Helenoides 6X, Histaminum Hydrochloricum 6X, 12X, 15X, 30X, Lac Caninum 6X, 12X, 15X, 30X, Glandula Suprarenalis Suis 8X, Mucosa Nasalis Suis 8X, Allium Cepa 12X, Arsenicum Album 12X, Blatta Americana 12X, Iridium Metallicum 12X, Sabadilla 12X, Selenium Metallicum 12X, Lac Felinum 12X 15X, 30X, Hyaluronidase 30X, Interferon (Suis) 30X, Serotonin (Hydrochloride) 30X, House Dust Mite 9C, 12C, 15C, 30C.

HOMEOPATHIC INDICATIONS:

For temporary relief of symptoms related to a reaction to pollens or dust including sneezing, congestion, stomach discomfort, lethargy and cough.**

**These statements are based upon traditional homeopathic principles. They have not been reviewed by the Food and Drug Administration.

WARNINGS:

Keep out of reach of children. In case of overdose, contact a physician or Poison Control Center right away.

If pregnant or breast-feeding, ask a health professional before use.

Tamper seal: "Sealed for Your Protection." Do not use if seal is broken or missing.

Keep out of reach of children. In case of overdose, contact a physician or Poison Control Center right away.

DIRECTIONS:

1-10 drops under the tongue, 3 times a day or as directed by a health professional. Consult a physician for use in children under 12 years of age.

HOMEOPATHIC INDICATIONS:

For temporary relief of symptoms related to a reaction to pollens or dust including sneezing, congestion, stomach discomfort, lethargy and cough.**

**These statements are based upon traditional homeopathic principles. They have not been reviewed by the Food and Drug Administration.

INACTIVE INGREDIENTS:

Demineralized Water, 25% Ethanol

QUESTIONS:

Dist. By: Deseret Biologicals, Inc.

469 W. Parkland Drive

Sandy, UT 84070 www.desbio.com

PACKAGE LABEL DISPLAY:

DESBIO

NDC 43742-0292-1

HOMEOPATHIC

PEST AND

DUSTMITE

FORMULA

1 FL OZ (30 ml)